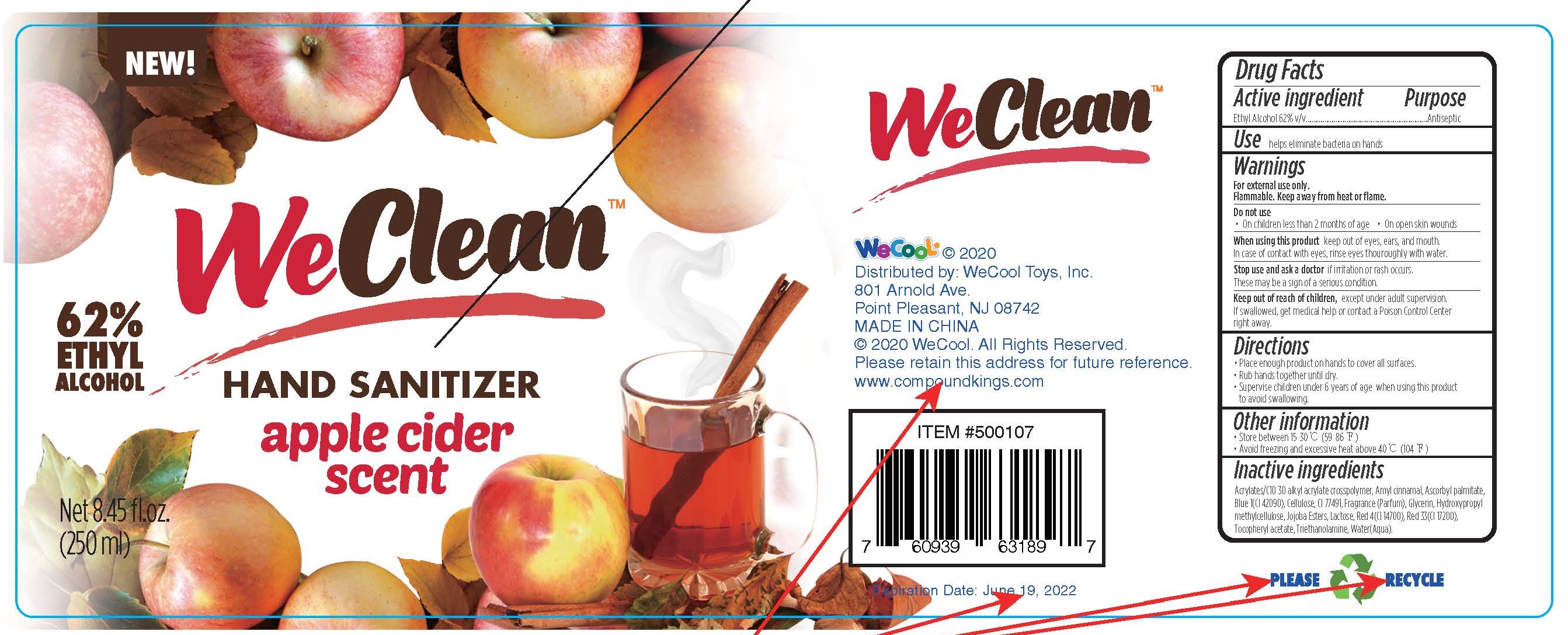 DRUG LABEL: WeClean Hand Sanitizer apple cider scent
NDC: 51706-924 | Form: GEL
Manufacturer: Landy International
Category: otc | Type: HUMAN OTC DRUG LABEL
Date: 20220321

ACTIVE INGREDIENTS: ALCOHOL 62 mL/100 mL
INACTIVE INGREDIENTS: CARBOMER COPOLYMER TYPE A (ALLYL PENTAERYTHRITOL CROSSLINKED); ASCORBYL PALMITATE; FD&C YELLOW NO. 5; POWDERED CELLULOSE; HYPROMELLOSES; TROLAMINE; JOJOBA OIL, RANDOMIZED; LACTOSE, UNSPECIFIED FORM; LIMONENE, (+)-; LINALOOL, (+/-)-; GLYCERIN; WATER; ALPHA-TOCOPHEROL ACETATE; FD&C RED NO. 4; GERANIOL; .ALPHA.-HEXYLCINNAMALDEHYDE

51706-924 WeClean Hand Sanitizer apple cider scent Ethyl Alcohol(62%)

Active Ingredient(s)

Ethyl Alcohol 62%

Purpose

Antiseptic

Use

helps eliminate bacteria on hands

Warnings

For external use only.
Flammable, Keep away from heat or flame,
Do not use
On children less than 2 months of age. on open skin wounds
When using this product keep out of eyes, ear, and mouth.
In case of contact with eve, rinse eyes thouroughly with water
Stop use and ask a doctor if irritation or rash occurs,
These may be a sign of a serious condition.

Keep out of reach of children. except under adult supervision.

If swallowed, get medical help or contact a poison control center right away.

Directions

Place enough product on hands to cover all surfaces.
Rub hands together until dry.
Supervise children under 6 years of age When using this product
to avoid swallowing.

Inactive ingredients

Acrlates/(10-30 alkyl acrylate crosspolymer, Ascorbyl palmitate, Cullose, Fragrance (parfum),
Geraniol, Glycerin, HexyI cinnamal, Hydroxypropyl methylcellulose, Jojoba Esters, Lactose,
Limonene, Linalool, Red 4(C(14700), Tocophery| acetate, Triethanolamine, Water(Aqua), Yellow 5(C| 19140).